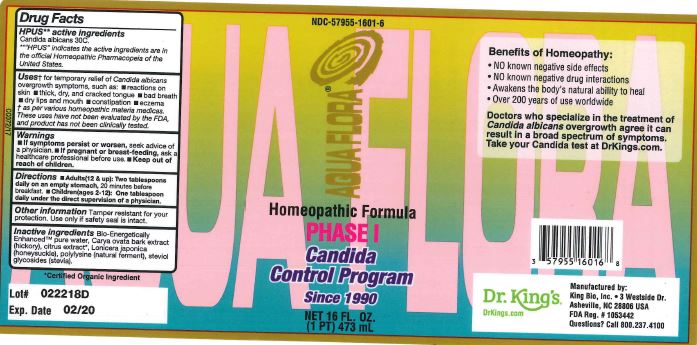 DRUG LABEL: Aquaflora Phase I
NDC: 57955-1601 | Form: LIQUID
Manufacturer: King Bio Inc
Category: homeopathic | Type: HUMAN OTC DRUG LABEL
Date: 20180320

ACTIVE INGREDIENTS: CANDIDA ALBICANS 30 [hp_C]/473 mL
INACTIVE INGREDIENTS: WATER; CARYA OVATA BARK; CITRUS BIOFLAVONOIDS; LONICERA JAPONICA FLOWER; POLYEPSILON-LYSINE (4000 MW); REBAUDIOSIDE A

Aquaflora Phase I

HPUS Active Ingredient

Candida albicans 30C

Uses

for temporary relief of Candida albicans overgrowt symptoms, such as:

- reactions on skin
- thick, dry, and cracked tongue
- bad breath
- dry lips and mouth
- constipation
- eczema

Warnings

If symptoms persist or worsen, seek advice of a physician

If pregnant or breast-feeding, ask a healthcare professional before use.

Keep out of reach of children

Directions

Adults (12 & up): Two tablespoons daily on an empty stomach, 20 minutes before breakfast.

Children(ages 2-12): One tablespoon daily under the direct supervision of a physician.

Other Information

Tamper resistant for your protection. Use only if safety seal is intact.

Purpose

for temporary relief of Candida albicans overgrowth symptoms, such as: reactions on skin, thick, dry and cracked tongue, bad breath, dry lips and mouth, constipation, eczema

Inactive Ingredients

Bio-Energetically Enhanced pure water, Carya ovata bark extract (hickory), citrus extract, Lonicera japonica (honeysuckle), polylysine (natural ferment), steviol glycosides (stevia).